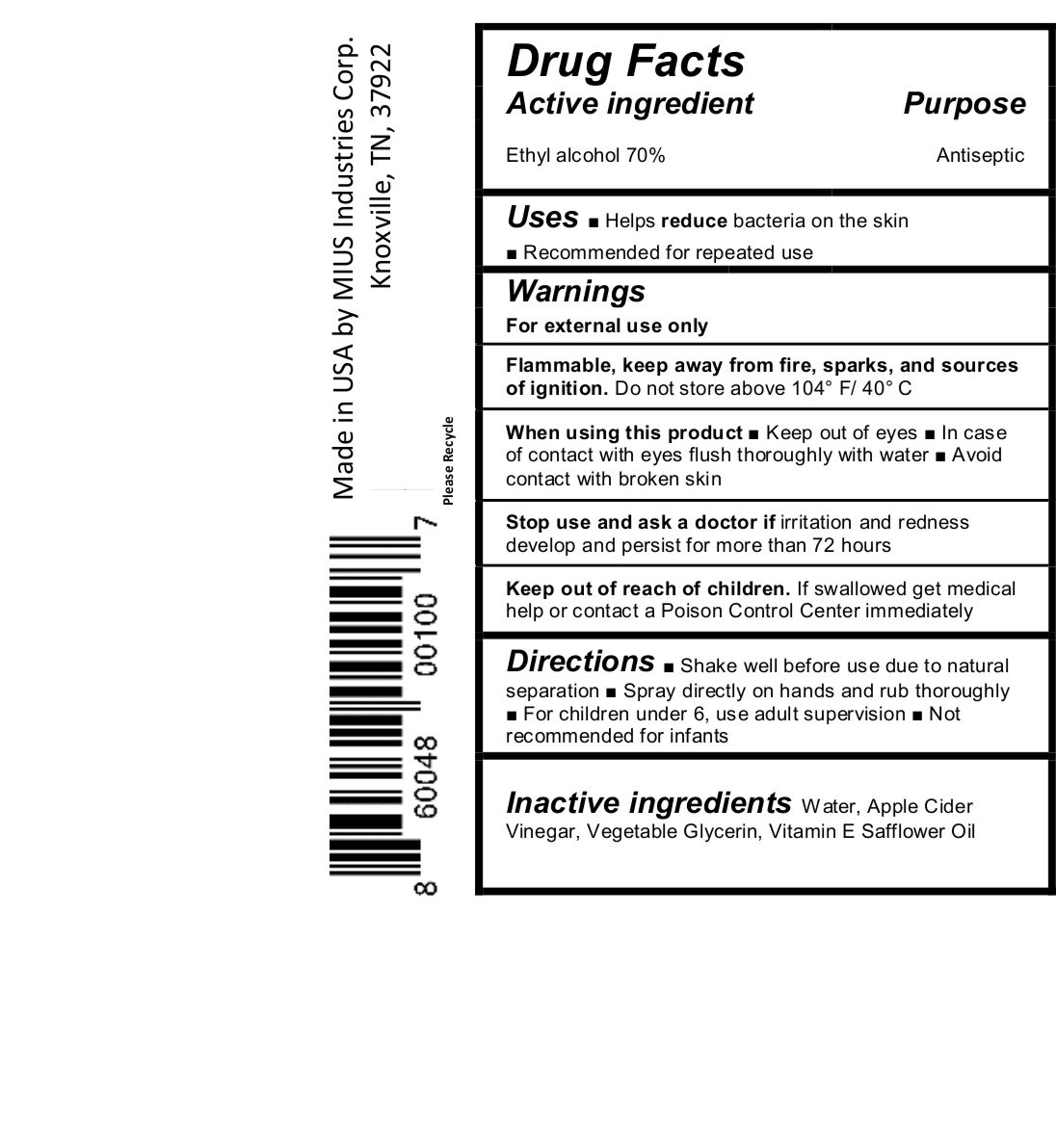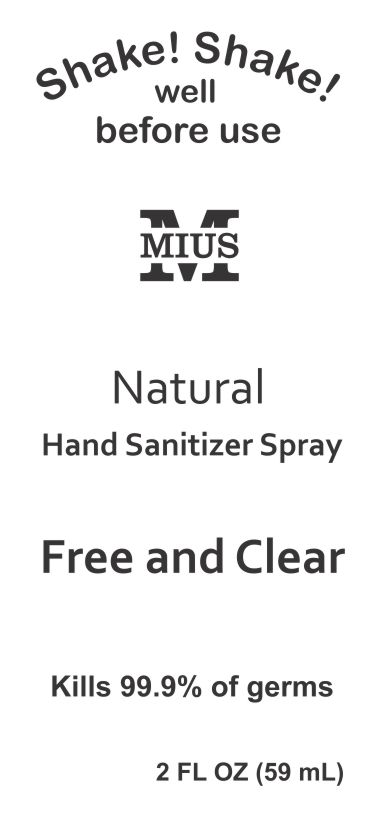 DRUG LABEL: MIUS
NDC: 71887-272 | Form: SPRAY
Manufacturer: MIUS Industries Corp.
Category: otc | Type: HUMAN OTC DRUG LABEL
Date: 20171226

ACTIVE INGREDIENTS: ALCOHOL 0.7 mL/1 mL
INACTIVE INGREDIENTS: GLYCERIN; APPLE CIDER VINEGAR; SAFFLOWER OIL; .ALPHA.-TOCOPHEROL ACETATE; WATER

MIUS Hand Sanitizer Free and Clear

Active Ingredient

Ethyl Alcohol 70%

Purpose

Antiseptic

Uses

■ Helps reduce bacteria on the skin

■ Recommended for repeated use

Warning

For External use only

Flammable, keep away from fire, sparks, and sources of ignition.

Do not store above 104° F/ 40° C

When using this product

■ Keep out of eyes ■ In case of contact with eyes flush thoroughly with water ■ Avoid contact with broken skin

Stop use and ask a doctor if

irritation and redness develop and persist for more than 72 hours

Keep out of reach of children.

If swallowed get medical help or contact a Poison Control Center immediately

Directions

■ Shake well before use due to natural separation ■ Spray directly on hands and rub thoroughly ■ For children under 6, use adult supervision ■ Not recommended for infants

Inactive ingredients

Water, Apple Cider Vinegar, Vegetable Glycerin, Vitamin E Safflower Oil